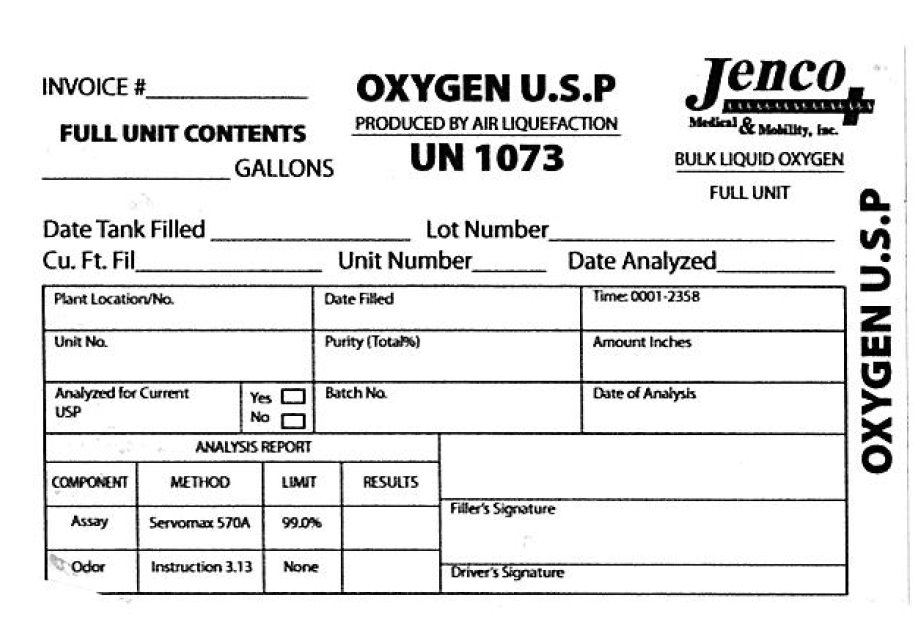 DRUG LABEL: Oxygen
NDC: 66988-100 | Form: GAS
Manufacturer: Jenco Medical and Mobility, Inc
Category: prescription | Type: HUMAN PRESCRIPTION DRUG LABEL
Date: 20100616

ACTIVE INGREDIENTS: OXYGEN 1 L/1 L

Oxygen U.S.P.

PACKAGE LABEL

Invoice OXYGEN U.S.P Jenco Medical and Mobility

Full Unit Contents Produced By Air Liquefaction Bulk Liquid Oxygen

Gallons UN 1073 Full Unit

Date Tank Filled Lot Number

Cu. Ft. Fil Unit Number Date Analyzed

Plant Location /No. Date Filled Time:0001-2358

Unit No. Purity Amount Inches

Analyzed for Current USP Batch No Date of Analysis

Analysis Report

Component Method Limit Results

Assay Servomax 570A 99.0 Percent

Odor Instruction 3.13 none

Filler's Signature

Driver's Signature